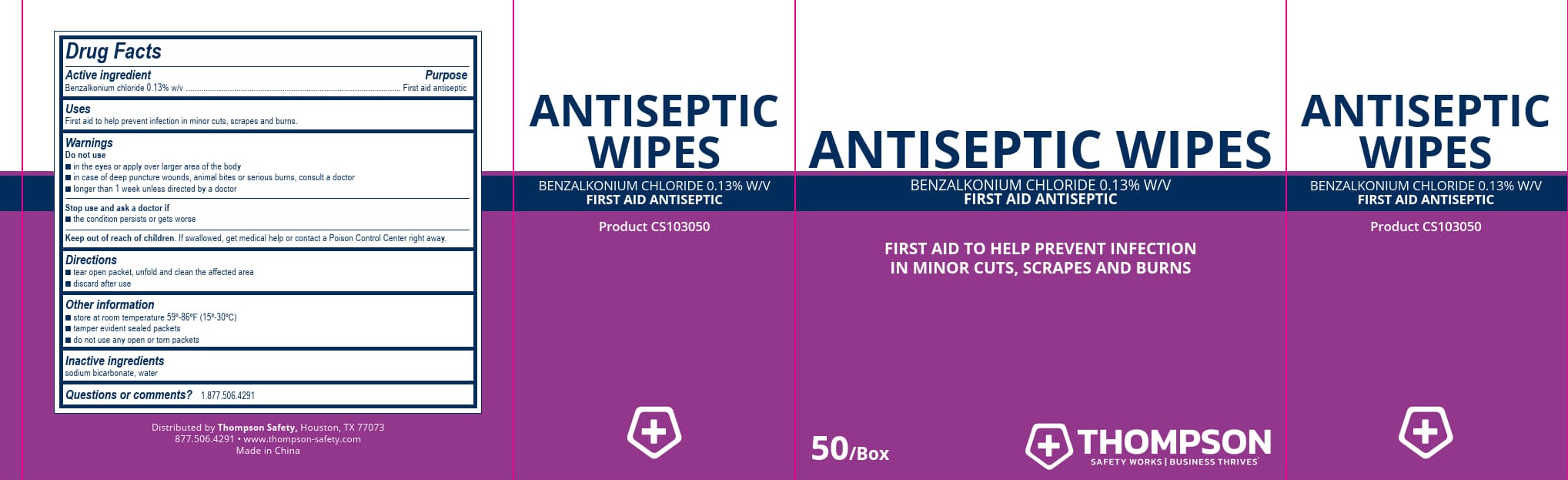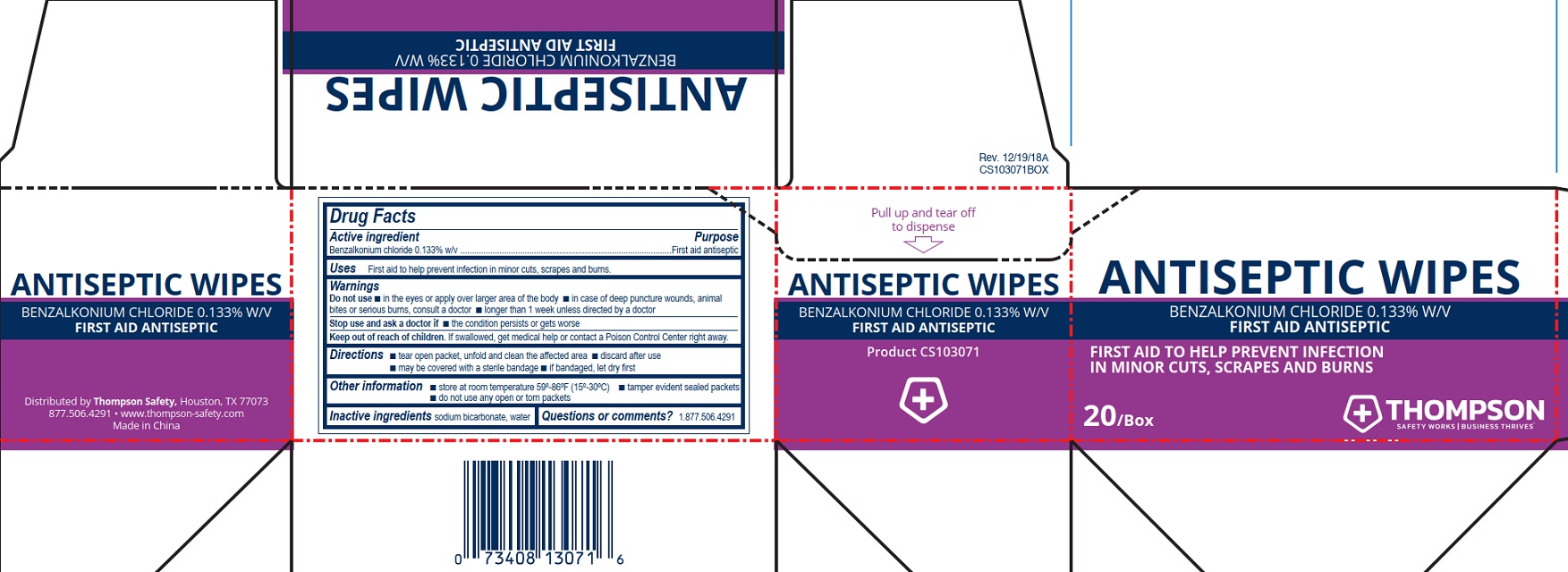 DRUG LABEL: Thompson Antiseptic
NDC: 73408-032 | Form: SWAB
Manufacturer: Thompson
Category: otc | Type: HUMAN OTC DRUG LABEL
Date: 20250909

ACTIVE INGREDIENTS: BENZALKONIUM CHLORIDE 1.33 mg/1 mL
INACTIVE INGREDIENTS: WATER; SODIUM BICARBONATE

Thompson Antiseptic Wipes

Drug Facts

Active ingredient

Benzalkonium chloride 0.13% w/v

Purpose

First aid antiseptic

Uses

First aid to help prevent infection in minor cuts, scrapes and burns.

Warnings

Do not use

- in the eyes or apply over larger area of the body
- in case of deep puncture wounds, aniamal bites or serious burns, consult a doctor
- longer than 1 week unless directed by a doctor

Stop use and ask a doctor if

- the condition persists or gets worse

Keep out of reach of children. If swallowed, get medical help or contact a Poison Control Center right away.

Directions

- tear open packet, unfold and clean the affected area
- discard after use

Other information

- store at room temperature 59º-86ºF (15º-30ºC)
- tamper evident sealed packets
- do not use any open or torn packets

Inactive ingredient

Inactive ingredients sodium bicarbonate, water

Questions or comments? 1.877.506.4291

PACKAGE LABEL

Antiseptic Wipes

Benzalkonium Chloride 0.133% w/v

First Aid Antiseptic

First aid to help prevent infection in minor cuts, scrapes and burns

20/Box

Thompson

Safety Works | Business Thrives™